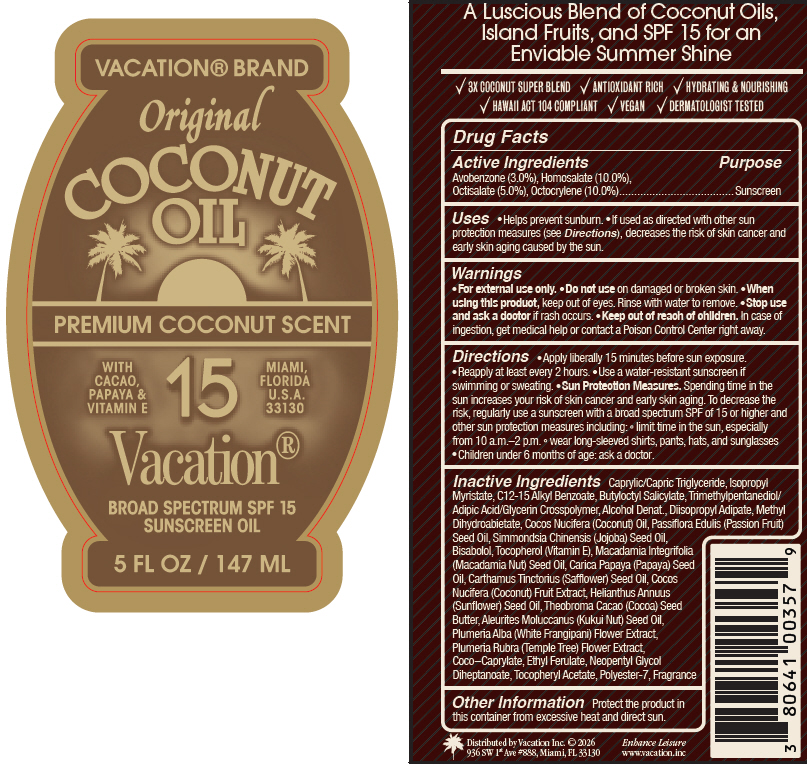 DRUG LABEL: Vacation Original Coconut SPF 15
NDC: 80641-620 | Form: OIL
Manufacturer: Vacation INC.
Category: otc | Type: HUMAN OTC DRUG LABEL
Date: 20260129

ACTIVE INGREDIENTS: AVOBENZONE 3 g/100 mL; Homosalate 10 g/100 mL; Octisalate 5 g/100 mL; Octocrylene 10 mg/100 mL
INACTIVE INGREDIENTS: ALCOHOL; Medium-Chain Triglycerides; Isopropyl Myristate; Alkyl (C12-15) Benzoate; Butyloctyl Salicylate; Diisopropyl Adipate; Coconut Oil; POLYESTER-8 (1400 MW, CYANODIPHENYLPROPENOYL CAPPED); PASSIFLORA EDULIS SEED OIL; Coco-Caprylate; Cocoa Butter; Coconut; Levomenol; Tocopherol; Safflower Oil; Macadamia Oil; KUKUI NUT OIL; Papaya Seed Oil; Sunflower Oil; PLUMERIA ALBA FLOWER OIL; .Alpha.-Tocopherol Acetate; FRAGRANCE 13576

Vacation® Original Coconut Oil SPF 15

Drug Facts

Active Ingredients

Avobenzone (3.0%), Homosalate (10.0%), Octisalate (5.0%), Octocrylene (10.0%)

Purpose

Sunscreen

Uses

- Helps prevent sunburn.
- If used as directed with other sun protection measures (see Directions), decreases the risk of skin cancer and early skin aging caused by the sun.

Warnings

- For external use only.

- Do not use on damaged or broken skin.

- When using this product, keep out of eyes. Rinse with water to remove.

- Stop use and ask a doctor if rash occurs.

- Keep out of reach of children. In case of ingestion, get medical help or contact a Poison Control Center right away.

Directions

- Apply liberally 15 minutes before sun exposure.
- Reapply at least every 2 hours.
- Use a water-resistant sunscreen if swimming or sweating.
- Sun Protection Measures. Spending time in the sun increases your risk of skin cancer and early skin aging. To decrease the risk, regularly use a sunscreen with a broad spectrum SPF of 15 or higher and other sun protection measures including:
  - limit time in the sun, especially from 10 a.m.–2 p.m.
  - wear long-sleeved shirts, pants, hats, and sunglasses
- Children under 6 months of age: ask a doctor.

Inactive Ingredients

Caprylic/Capric Triglyceride, Isopropyl Myristate, C12-15 Alkyl Benzoate, Butyloctyl Salicylate, Trimethylpentanediol/Adipic Acid/Glycerin Crosspolymer, Alcohol Denat., Diisopropyl Adipate, Methyl Dihydroabietate, Cocos Nucifera (Coconut) Oil, Passiflora Edulis (Passion Fruit) Seed Oil, Simmondsia Chinensis (Jojoba) Seed Oil, Bisabolol, Tocopherol (Vitamin E), Macadamia Integrifolia (Macadamia Nut) Seed Oil, Carica Papaya (Papaya) Seed Oil, Carthamus Tinctorius (Safflower) Seed Oil, Cocos Nucifera (Coconut) Fruit Extract, Helianthus Annuus (Sunflower) Seed Oil, Theobroma Cacao (Cocoa) Seed Butter, Aleurites Moluccanus (Kukui Nut) Seed Oil, Plumeria Alba (White Frangipani) Flower Extract, Plumeria Rubra (Temple Tree) Flower Extract, Coco-Caprylate, Ethyl Ferulate, Neopentyl Glycol Diheptanoate, Tocopheryl Acetate, Polyester-7, Fragrance

Other Information

Protect the product in this container from excessive heat and direct sun.

Distributed by Vacation Inc.
936 SW 1st Ave #888, Miami, FL 33130

PRINCIPAL DISPLAY PANEL - 147 ML Bottle Label

VACATION® BRAND

Original

COCONUT
OIL

PREMIUM COCONUT SCENT

WITH
CACAO,
PAPAYA &
VITAMIN E

15

MIAMI,
FLORIDA
U.S.A.
33130

Vacation®

BROAD SPECTRUM SPF 15
SUNSCREEN OIL

5 FL OZ / 147 ML